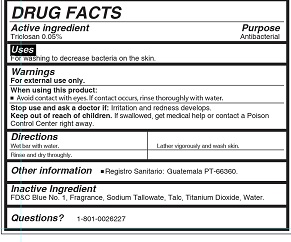 DRUG LABEL: Jabonito Fresh
NDC: 62476-100 | Form: SOAP
Manufacturer: Industria LA Popular SA
Category: otc | Type: HUMAN OTC DRUG LABEL
Date: 20160216

ACTIVE INGREDIENTS: TRICLOSAN 0.0005 g/1 g
INACTIVE INGREDIENTS: TITANIUM DIOXIDE; SODIUM TALLOWATE, BEEF; TALC; ABRONIA FRAGRANS WHOLE; WATER

PURPOSE

Antibacterial

For washing to decrease bacteria on the skin.

ACTIVE INGREDIENT

Triclosan 0.05%

WARNING

For external use only

WHEN USING THIS PRODUCT

Avoid contact with eyes. If contact occurs rinse thoroughly with water.

STOP USE and contact doctor if irritation and redness develops.

KEEP OUT OF REACH OF CHILDREN

If swallowed, get medical help or contact poison control center right away.

DIRECTIONS

Wet bar with water.

Lather vigirously and wash skin.

Rinse and dry thoroughly.

INACTIVE INGREDIENTS

Titanium Dioxide
Water
Talc
Fragrance
Sodium Tallowate

FD & C Blue No.1

OTHER INFORMATION

Registro sanitario: Guatemala PT-66360

QUESTIONS?

1-801-0026-227

Dosage and Administration